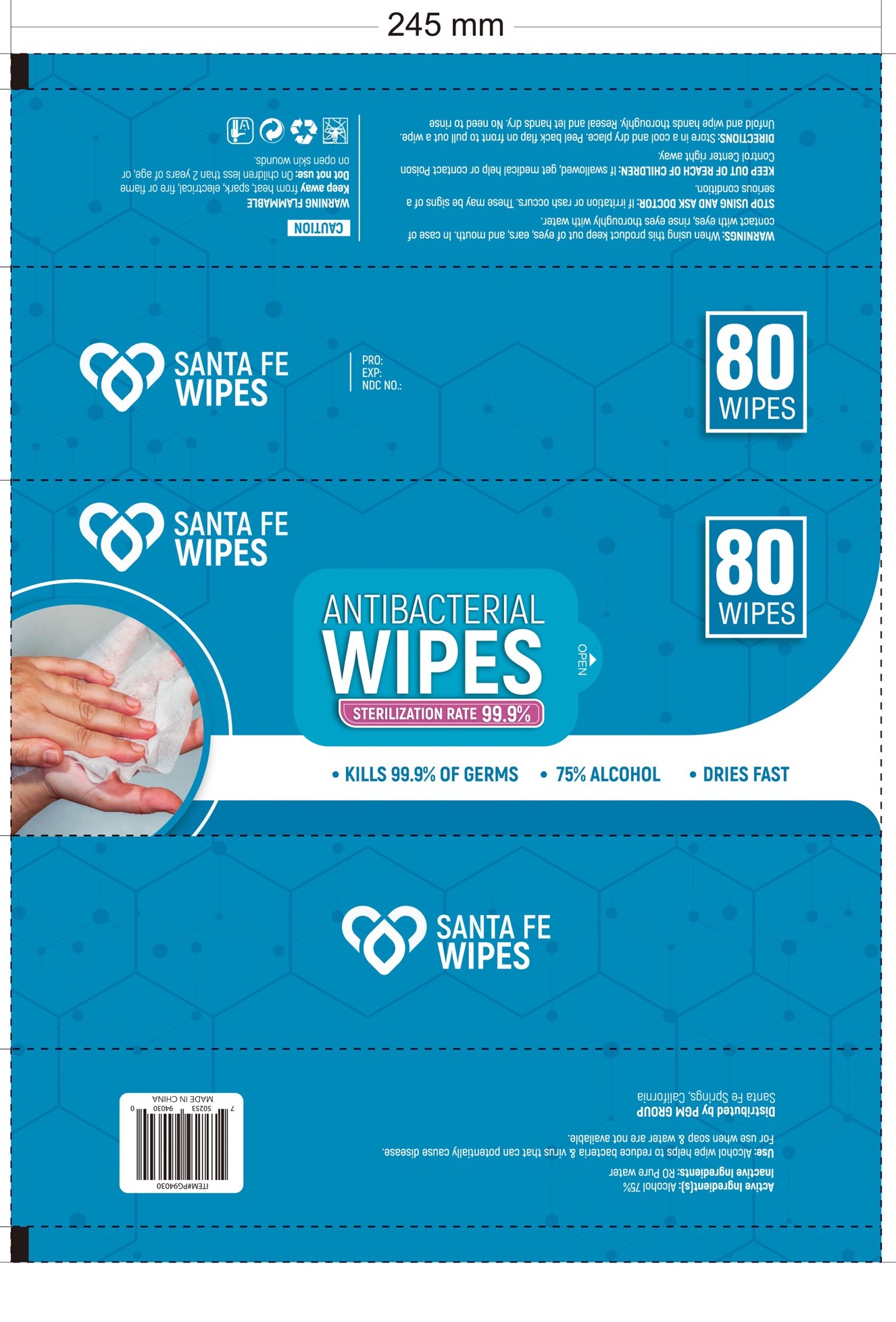 DRUG LABEL: Alcohol wipes
NDC: 78356-202 | Form: CLOTH
Manufacturer: Zhejiang Yiwu Anrou Sanitation Article Co., Ltd
Category: otc | Type: HUMAN OTC DRUG LABEL
Date: 20200720

ACTIVE INGREDIENTS: ALCOHOL 3.125 mL/1 1
INACTIVE INGREDIENTS: WATER

Anrou-PGM, Alcohol wipes, 75% Alcohol

Active ingredient

Alcohol 75% v/v. Purpose: Antibacterial

Purpose

Antibacterial

When Using

When using this product keep out of eyes, ears, and mouth.

In case of contact with eyes, rinse eyes throughly with water.

Do not use

On children less than 2 years of age, or on open skin wounds.

Stop use

Stop using and ask a doctor: If irritation or rash occurs. These may be signs of a serious condition.

KEEP OUT OF REACH OF CHILDREN

If swallowed, get medical help or contact Poison Control Center right away.

Indications & usage

Alcohol wipe helps to reduce bacteria & virus that can potentially cause disease.

For use when soap and water are not available.

Directions

Peel back flap on front to pull out a wipe.

Unfold and wipe hands thoroughly.

Reseal and let hands dry.

No need to rinse.

Warnings

WARNING FLAMMABLE

Keep away from heat, spark, electrical, fire or flame.

Other information

Store in a cool and dry place.

Inactive ingredient

RO Pure water.